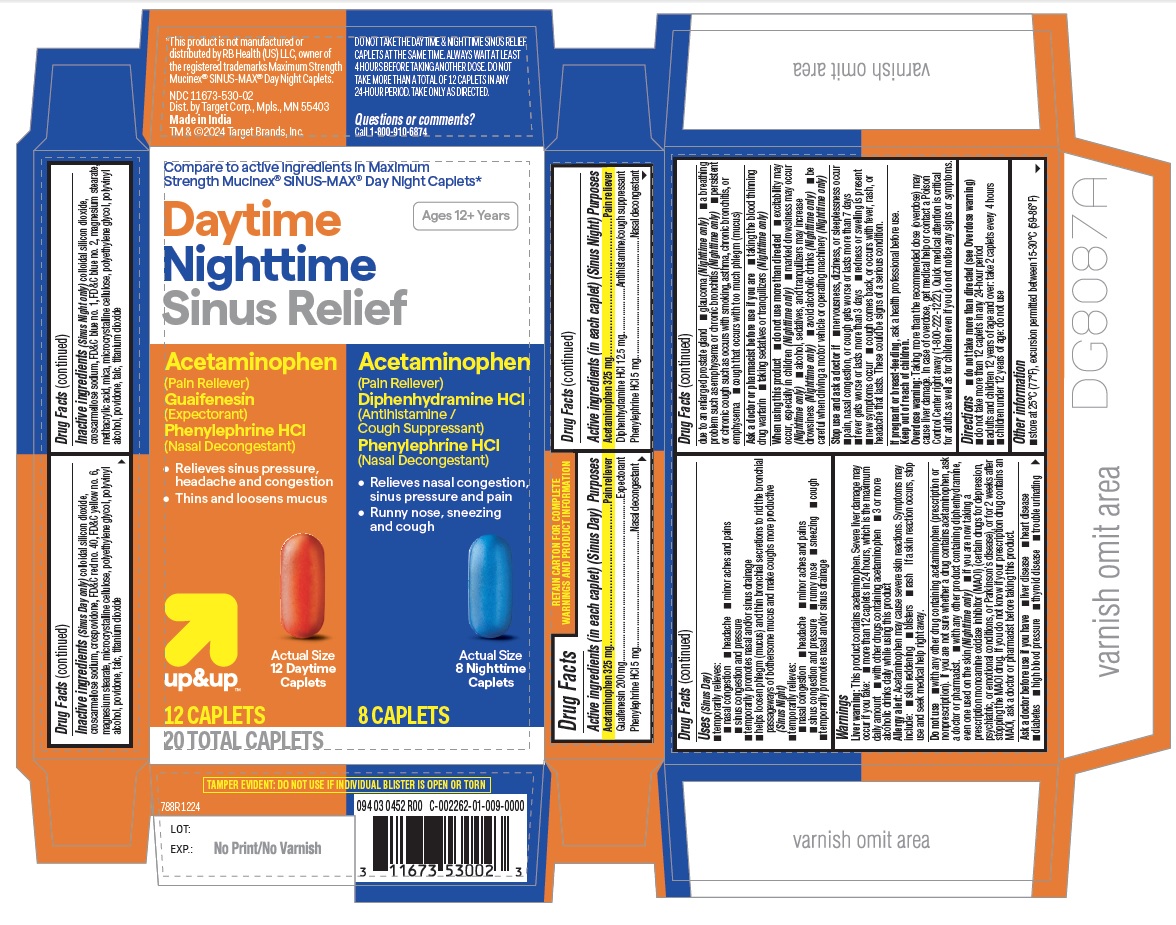 DRUG LABEL: Daytime Nighttime Sinus Relief
NDC: 11673-530 | Form: KIT | Route: ORAL
Manufacturer: Target Corporation
Category: otc | Type: HUMAN OTC DRUG LABEL
Date: 20250614

ACTIVE INGREDIENTS: ACETAMINOPHEN 325 mg/1 1; PHENYLEPHRINE HYDROCHLORIDE 5 mg/1 1; GUAIFENESIN 200 mg/1 1; ACETAMINOPHEN 325 mg/1 1; DIPHENHYDRAMINE HYDROCHLORIDE 12.5 mg/1 1; PHENYLEPHRINE HYDROCHLORIDE 5 mg/1 1
INACTIVE INGREDIENTS: CROSCARMELLOSE SODIUM; SILICON DIOXIDE; CROSPOVIDONE, UNSPECIFIED; MAGNESIUM STEARATE; MICROCRYSTALLINE CELLULOSE; POVIDONE, UNSPECIFIED; CROSCARMELLOSE SODIUM; MAGNESIUM STEARATE; MICROCRYSTALLINE CELLULOSE; POVIDONE, UNSPECIFIED; SILICON DIOXIDE

788R Target Daytime Nighttime Sinus Relief

Active ingredients (in each caplet) (Sinus Day)

Acetaminophen 325 mg
Guaifenesin 200 mg
Phenylephrine HCl 5 mg

Purpose

Pain reliever
Expectorant
Nasal decongestant

Active ingredients (in each caplet) (Sinus Night)

Acetaminophen 325 mg
Diphenhydramine HCl 12.5 mg
Phenylephrine HCl 5 mg

Purpose

Pain reliever
Antihistamine/cough suppressant
Nasal decongestant

Uses

- temporarily relieves these common cold symptoms:
  - nasal congestion
  - headache
  - minor aches and pains
  - sinus congestion and pressure
  - cough (Nighttime only)
  - runny nose and sneezing (Nighttime only)
- temporarily promotes nasal and/or sinus drainage
- helps loosen phlegm (mucus) and thin bronchial secretions to rid the bronchial passageways of bothersome mucus and make coughs more productive (Daytime only)

Warnings

Liver warning:This product contains acetaminophen. Severe liver damage may occur if you take

- more than 4,000 mg of acetaminophen in 24 hours
- with other drugs containing acetaminophen
- 3 or more alcoholic drinks every day while using this product

Allergy alert:Acetaminophen may cause severe skin reactions. Symptoms may include:

- skin reddening
- blisters
- rash

If a skin reaction occurs, stop use and seek medical help right away.

Do not use

- with any other drug containing acetaminophen (prescription or nonprescription). If you are not sure whether a drug contains acetaminophen, ask a doctor or pharmacist.
- if you are now taking a prescription monoamine oxidase inhibitor (MAOI) (certain drugs for depression, psychiatric, or emotional conditions, or Parkinson’s disease), or for 2 weeks after stopping the MAOI drug. If you do not know if your prescription drug contains an MAOI, ask a doctor or pharmacist before taking this product.
- if you have ever had an allergic reaction to this product or any of its ingredients
- with any other product containing diphenhydramine, even one used on skin (Nighttime only)

Ask a doctor before use if you have

- heart disease
- liver disease
- diabetes
- thyroid disease
- high blood pressure
- difficulty in urination due to enlargement of the prostate gland
- persistent or chronic cough such as occurs with smoking, asthma, chronic bronchitis, or emphysema
- cough that occurs with too much phlegm (mucus)
- a breathing problem such as emphysema or chronic bronchitis (Nighttime only)
- glaucoma (Nighttime only)

Ask a doctor or pharmacist before use if you are

- taking the blood thinning drug warfarin
- taking sedatives or tranquilizers (Nighttime only)

When using this product

- do not exceed recommended dosage
- excitability may occur, especially in children (Nighttime only)
- marked drowsiness may occur (Nighttime only)
- alcohol, sedatives, and tranquilizers may increase drowsiness (Nighttime only)
- avoid alcoholic beverages (Nighttime only)
- use caution when driving a motor vehicle or operating machinery (Nighttime only)

Stop use and ask a doctor if

- nervousness, dizziness, or sleeplessness occur
- pain, nasal congestion, or cough gets worse or lasts more than 7 days
- fever gets worse or lasts more than 3 days
- redness or swelling is present
- new symptoms occur
- cough comes back or occurs with rash or headache that lasts. These could be signs of a serious condition.

If pregnant or breast-feeding,

ask a health professional before use.

Keep out of reach of children.

In case of overdose, get medical help or contact a Poison Control Center right away. Prompt medical attention is critical for adults as well as for children even if you do not notice any signs or symptoms.

Do not take DAYTIME and NIGHTTIME products at the same time.

Directions

- do not take more than directed
- do not take more than 12 caplets in any 24-hour period
- adults and children 12 years and over: take 2 caplets every 4 hours
- children under 12 years: do not use

Other information

- store at 25°C(77°F), excursion permitted between 15-30°C (59-86°F)

Inactive ingredients (Daytime only)

Inactive ingredients (Sinus Day only)

colloidal silicon dioxide, croscarmellose sodium, crospovidone, FD&C red no. 40, FD&C yellow no. 6, magnesium stearate, microcrystalline cellulose, polyethylene glycol, polyvinyl alcohol, povidone, talc, titanium dioxide

Inactive ingredients (Nighttime only)

Inactive ingredients (Sinus Night only)

colloidal silicon dioxide, croscarmellose sodium, FD&C blue no. 1, FD&C blue no. 2 magnesium stearate, methacrylic acid, mica, microcrystalline cellulose, polyethylene glycol, polyvinyl alcohol, povidone, talc, titanium dioxide

Questions or comments?

Call 1-800-910-6874